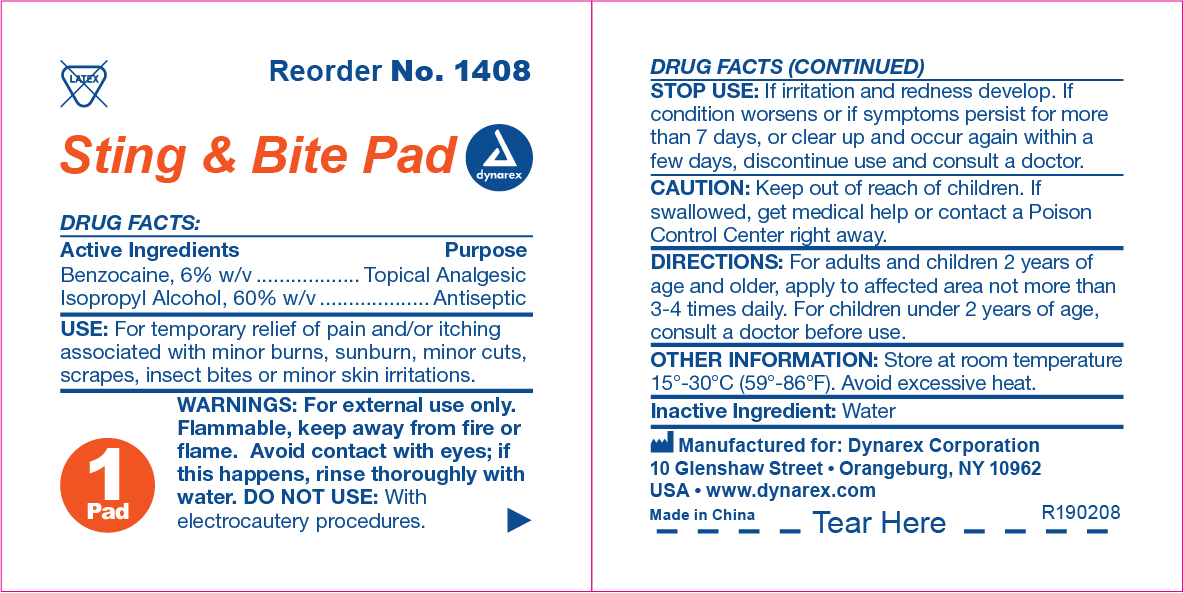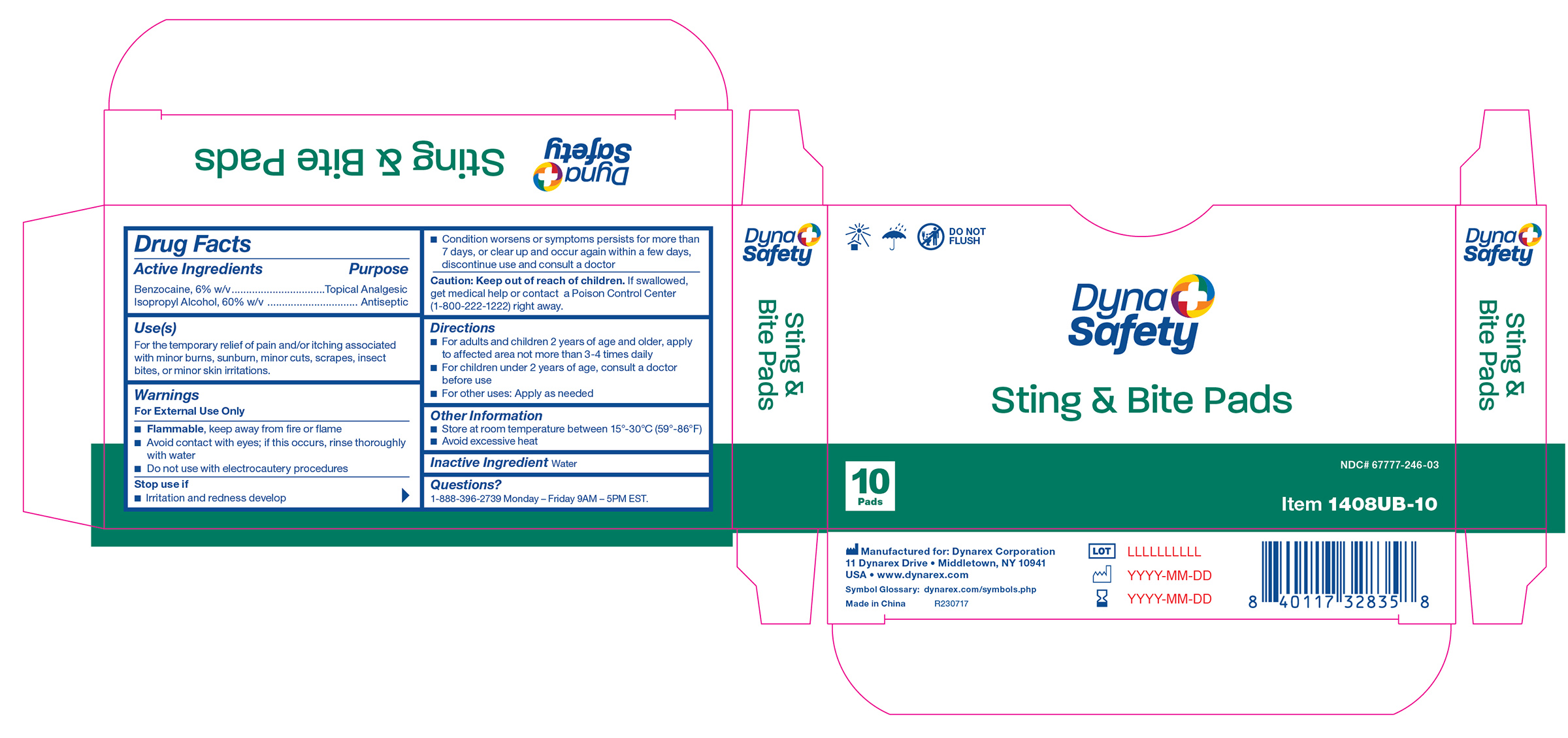 DRUG LABEL: Benzocaine
NDC: 67777-246 | Form: SWAB
Manufacturer: Dynarex Corporation
Category: otc | Type: HUMAN OTC DRUG LABEL
Date: 20260106

ACTIVE INGREDIENTS: ISOPROPYL ALCOHOL 60 mg/100 mL; BENZOCAINE 6 mg/100 mL
INACTIVE INGREDIENTS: WATER

1408 Sting & Bite Pad 67777-246-01

Active Ingredient

Benzocaine, 6% w/v

Purpose

Topical Analgesic

Active Ingredient

Isopropyl Alcohol, 60% w/v

Purpose

Antiseptic

Use(s)

For the temporary relief of pain and/or itching associated with minor burns, sunburn, minor cuts, scrapes, insect bites, or minor skin irritations.

Warnings

For External Use Only

• Flammable, keep away from fire or flame

• Avoid contact with eyes; if this occures, rinse thoroughly with water

• Do not use with electrocautery procedures

Stop use if

• Irritation and redness develop

• Condition worsens or symptoms persists for more than 7 days, or clear up and occur again within a few days, discontinue use and consult a doctor

Keep out of reach of children

If swallowed, get medical help or contact a Poison Control Center (1-800-222-1222) right away.

Directions

- For adults and children 2 years of age and older: Apply to affected area not more than 3-4 times daily.
- Children under 2 years: Consult a physician before use
- For other uses: Apply as needed

Other Information

• Store at room temperature between 15º-30ºC (59º-86ºF)

• Avoid excessive heat

Inactive Ingredients

Water

Questions?

1-888-396-2739 Monday - Friday 9AM-5PM EST.

Label

Sting & Bite Pad Label

Label 1408UB-10

1408UB-10